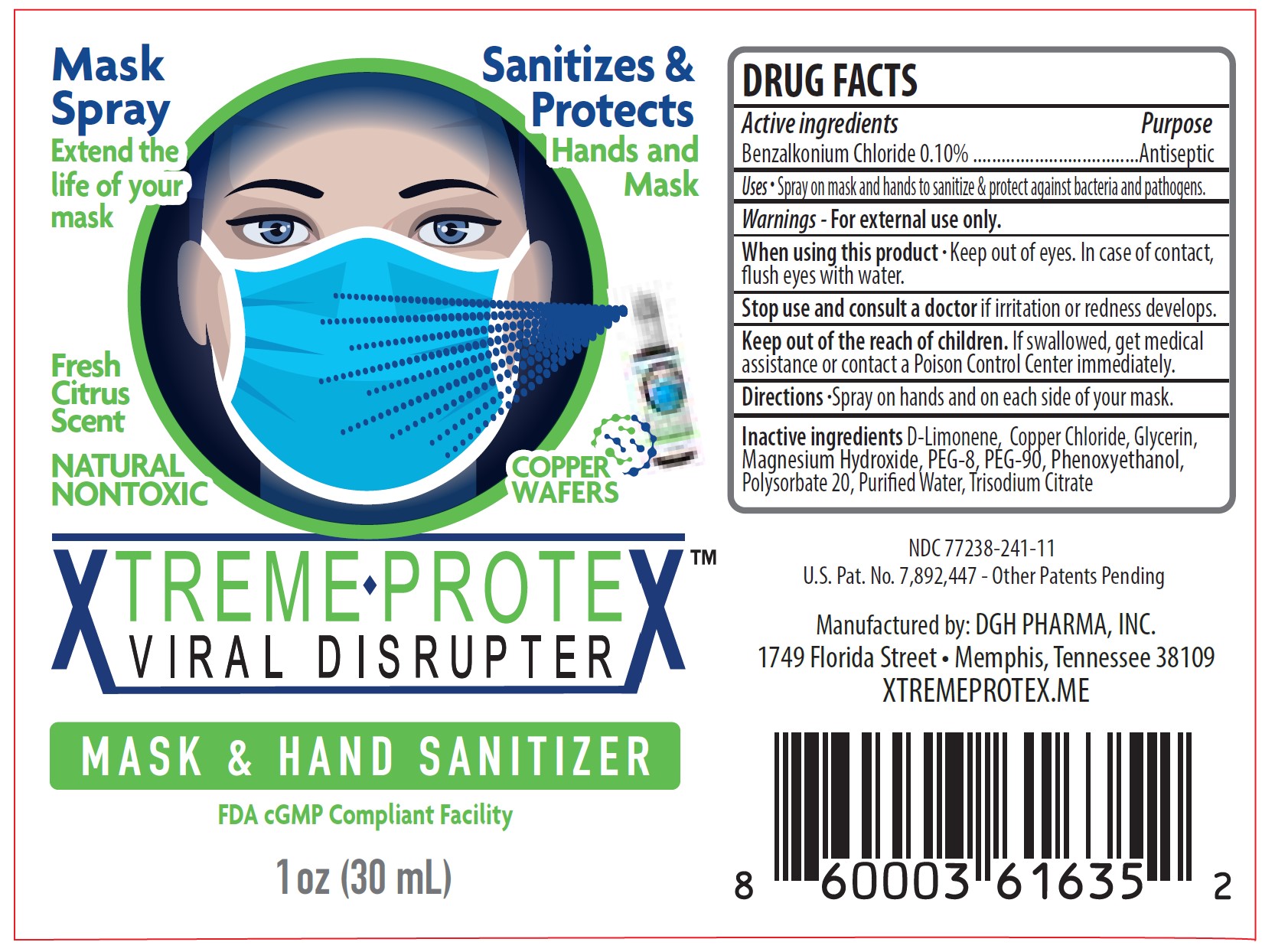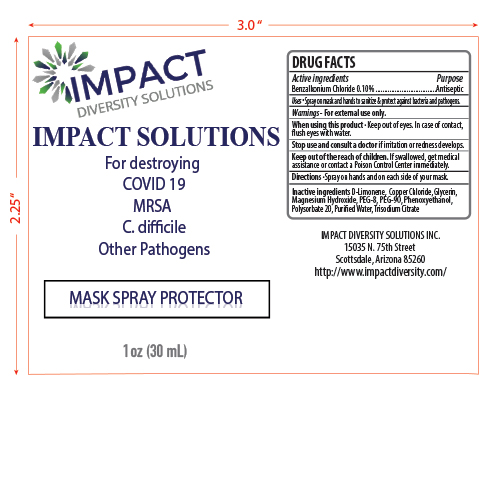 DRUG LABEL: Hand Sanitizer
NDC: 77238-241 | Form: SPRAY
Manufacturer: DGH Pharma, Inc.
Category: otc | Type: HUMAN OTC DRUG LABEL
Date: 20220729

ACTIVE INGREDIENTS: BENZALKONIUM CHLORIDE 0.1 g/100 mL
INACTIVE INGREDIENTS: POLYETHYLENE GLYCOL 4000 2.2 g/100 mL; POLYETHYLENE GLYCOL 400 0.21 g/100 mL; WATER; GLYCERIN 0.21 g/100 mL; POLYSORBATE 20 0.2 g/100 mL; PHENOXYETHANOL 0.4 g/100 mL; MAGNESIUM HYDROXIDE 0.005 g/100 mL; CUPRIC CHLORIDE 0.267 g/100 mL; LIMONENE, (+)- 0.1 g/100 mL; ANHYDROUS TRISODIUM CITRATE 0.15 g/100 mL

Hand Sanitizer Spray - 32016

Active Ingredient(s)

Benzalkonium Chloride 0.10% w/w. Purpose: Antiseptic

Purpose

Antiseptic, Hand Sanitizer

Use

Spray on mask and hands to sanitize & protect against bacteria and pathogens.

Warnings

For external use only.

When using this product keep out of eyes. In case of contact, flush eyes with water.
Stop use and ask a doctor if irritation or redness develops
Keep out of reach of children. If swallowed, get medical assistance or contact a Poison Control Center immediately.

Stop use and ask a doctor if irritation or redness develops.

Keep out of reach of children. If swallowed, get medical assistance or contact a Poison Control Center immediately.

Directions

- Spray on hands and on each side of your mask

Inactive ingredients

D-Limonene, Copper Chloide, Glycerin, Magnesium Hydroxide, PEG-8, PEG-90, Phenoxyethanol, Polysorbate 20, Purified Water, Trisodium Citrate